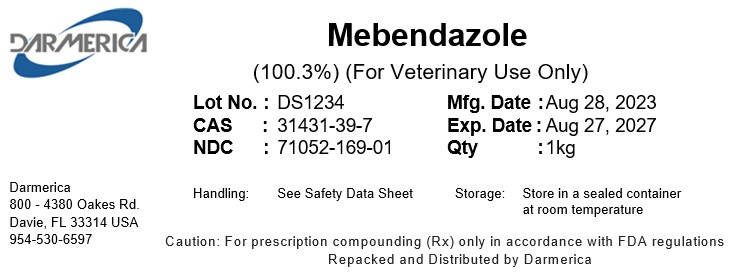 DRUG LABEL: Mebendazole
NDC: 71052-169 | Form: POWDER
Manufacturer: DARMERICA, LLC
Category: other | Type: BULK INGREDIENT - ANIMAL DRUG
Date: 20250422

ACTIVE INGREDIENTS: MEBENDAZOLE 1 kg/1 kg

Mebendazole